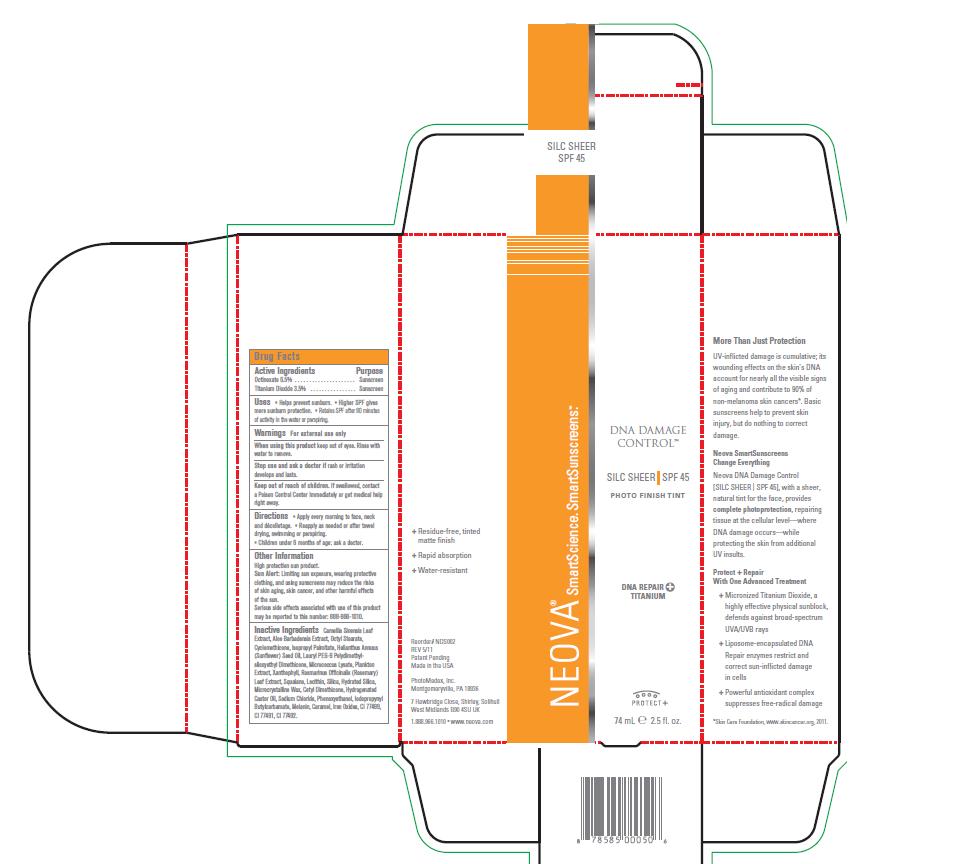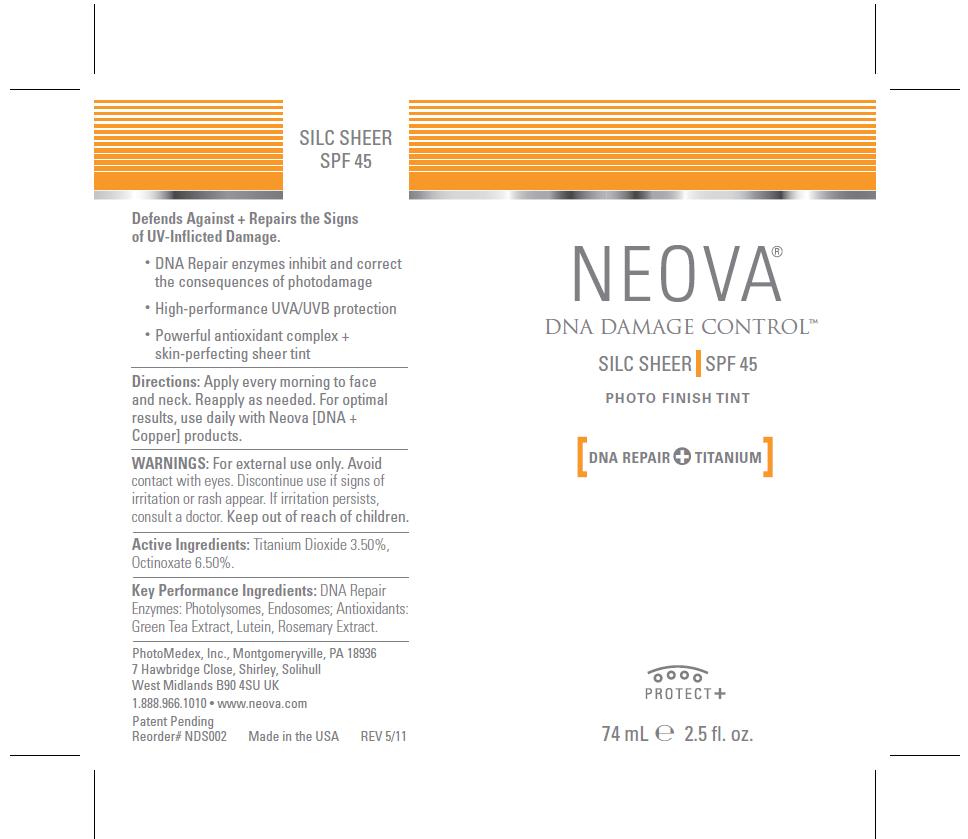 DRUG LABEL: Neova DNA Damage Control - Silc Sheer
NDC: 62362-149 | Form: EMULSION
Manufacturer: PhotoMedex, Inc.
Category: otc | Type: HUMAN OTC DRUG LABEL
Date: 20120106

ACTIVE INGREDIENTS: Octinoxate 6.5 mL/100 mL; Titanium Dioxide 3.5 mL/100 mL
INACTIVE INGREDIENTS: Green Tea Leaf; Aloe Vera Leaf; Octyl Stearate; Cyclomethicone; Isopropyl Palmitate; Sunflower Oil; Lutein; Rosemary; Squalane; Egg Phospholipids; Silicon Dioxide; Hydrated Silica; Microcrystalline Wax; Hydrogenated Castor Oil; Sodium Chloride; Phenoxyethanol; Iodopropynyl Butylcarbamate; Caramel; Ferrosoferric Oxide; Ferric Oxide Red; Ferric Oxide Yellow

Neova DNA Damage Control - Silc Sheer SPF 45 - Drug Facts

Active Ingredients

Octinoxate 6.5%, Titanium Dioxide 3.5%

Purpose

Sunscreen

Uses

• Helps prevent sunburn. • Higher SPF gives
more sunburn protection. • Retains SPF after 80 minutes
of activity in the water or perspiring.

Warnings

For external use only

When using this product:

Keep out of eyes. Rinse with water to remove.

Stop use and ask a doctor if:

Rash or irritation develops and lasts.

Keep out of reach of children:

If swallowed, contact a Poison Control Center immediately or get medical help right away.

Directions

• Apply every morning to face, neck
and décolletage. • Reapply as needed or after towel
drying, swimming or perspiring.
• Children under 6 months of age: ask a doctor.

Other Information

High protection sun product. Sun Alert: Limiting sun exposure, wearing protective clothing, and using sunscreens may reduce the risks of skin aging, skin cancer, and other harmful effects of the sun. Serious side effects associated with use of this product may be reported to this number: 888-966-1010.

Inactive Ingredients

Camellia Sinensis Leaf
Extract, Aloe Barbadensis Extract, Octyl Stearate,
Cyclomethicone, Isopropyl Palmitate, Helianthus Annuus
(Sunflower) Seed Oil, Lauryl PEG-9 Polydimethylsiloxyethyl
Dimethicone, Micrococcus Lysate, Plankton
Extract, Xanthophyll, Rosmarinus Officinalis (Rosemary)
Leaf Extract, Squalane, Lecithin, Silica, Hydrated Silica,
Microcrystalline Wax, Cetyl Dimethicone, Hydrogenated
Castor Oil, Sodium Chloride, Phenoxyethanol, Iodopropynyl
Butylcarbamate, Melanin, Caramel, Iron Oxides, CI 77499,
CI 77491, CI 77492.

Image of box and label

DNADControlSHEERBox.jpg DNADControlSHEERLabel.jpg